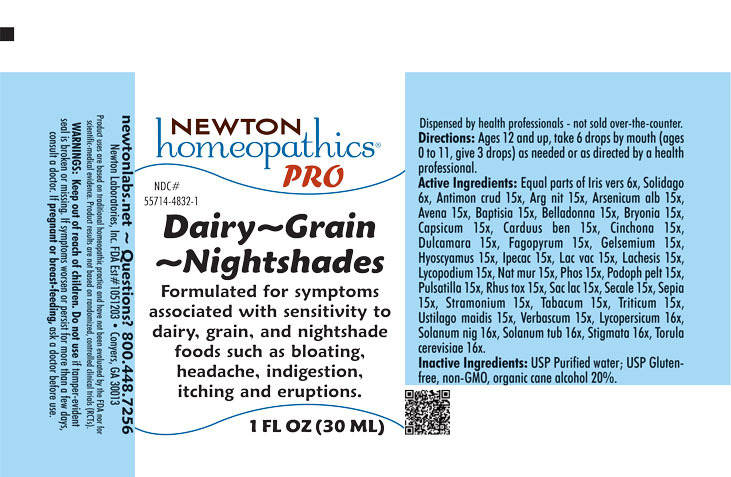 DRUG LABEL: Dairy-Grain-Nightshade
NDC: 55714-4832 | Form: LIQUID
Manufacturer: Newton Laboratories, Inc.
Category: homeopathic | Type: HUMAN OTC DRUG LABEL
Date: 20250725

ACTIVE INGREDIENTS: IRIS VERSICOLOR ROOT 6 [hp_X]/1 mL; AVENA SATIVA FLOWERING TOP 15 [hp_X]/1 mL; CAPSICUM 15 [hp_X]/1 mL; CENTAUREA BENEDICTA 15 [hp_X]/1 mL; CINCHONA OFFICINALIS BARK 15 [hp_X]/1 mL; CORN SILK 16 [hp_X]/1 mL; ANTIMONY TRISULFIDE 15 [hp_X]/1 mL; TOXICODENDRON PUBESCENS LEAF 15 [hp_X]/1 mL; HYOSCYAMUS NIGER 15 [hp_X]/1 mL; IPECAC 15 [hp_X]/1 mL; ELYMUS REPENS ROOT 15 [hp_X]/1 mL; LACHESIS MUTA VENOM 15 [hp_X]/1 mL; SOLANUM DULCAMARA TOP 15 [hp_X]/1 mL; BRYONIA ALBA ROOT 15 [hp_X]/1 mL; FAGOPYRUM ESCULENTUM 15 [hp_X]/1 mL; GELSEMIUM SEMPERVIRENS ROOT 15 [hp_X]/1 mL; DATURA STRAMONIUM 15 [hp_X]/1 mL; USTILAGO MAYDIS 15 [hp_X]/1 mL; SOLANUM LYCOPERSICUM 16 [hp_X]/1 mL; ARSENIC TRIOXIDE 15 [hp_X]/1 mL; SOLANUM TUBEROSUM 16 [hp_X]/1 mL; SACCHAROMYCES CEREVISIAE 16 [hp_X]/1 mL; CLAVICEPS PURPUREA SCLEROTIUM 15 [hp_X]/1 mL; SOLIDAGO VIRGAUREA FLOWERING TOP 6 [hp_X]/1 mL; SILVER NITRATE 15 [hp_X]/1 mL; ATROPA BELLADONNA 15 [hp_X]/1 mL; TOBACCO LEAF 15 [hp_X]/1 mL; SEPIA OFFICINALIS JUICE 15 [hp_X]/1 mL; PHOSPHORUS 15 [hp_X]/1 mL; BAPTISIA TINCTORIA ROOT 15 [hp_X]/1 mL; LYCOPODIUM CLAVATUM SPORE 15 [hp_X]/1 mL; SODIUM CHLORIDE 15 [hp_X]/1 mL; ANEMONE PULSATILLA 15 [hp_X]/1 mL; LACTOSE, UNSPECIFIED FORM 15 [hp_X]/1 mL; PODOPHYLLUM 15 [hp_X]/1 mL; VERBASCUM THAPSUS 15 [hp_X]/1 mL; SOLANUM NIGRUM WHOLE 16 [hp_X]/1 mL; COW MILK 15 [hp_X]/1 mL
INACTIVE INGREDIENTS: WATER; ALCOHOL

Dairy 4832L

INDICATIONS & USAGE SECTION

Formulated for symptoms associated with sensitivity and intolerance to dairy, grain and nightshade foods such as bloating, headache, indigestion, itching and eruptions.

DOSAGE & ADMINISTRATION SECTION

Directions: Ages 12 and up, take 6 drops by mouth (ages 0 to 11, give 3 drops) as needed or as directed by a health professional.

OTC - ACTIVE INGREDIENT SECTION

Equal parts of Iris versicolor 6x, Solidago virgaurea 6x, Antimonium crudum 15x, Argentum nitricum 15x, Arsenicum album 15x, Avena sativa 15x, Baptisia tinctoria 15x, Belladonna 15x, Bryonia 15x, Capsicum annuum 15x, Carduus benedictus 15x, Cinchona officinalis 15x, Dulcamara 15x, Fagopyrum esculentum 15x, Gelsemium sempervirens 15x, Hyoscyamus niger 15x, Ipecacuanha 15x, Lac vaccinum 15x, Lachesis mutus 15x, Lycopodium clavatum 15x, Natrum muriaticum 15x, Phosphorus 15x, Podophyllum peltatum 15x, Pulsatilla 15x, Rhus toxicodendron 15x, Saccharum lactis 15x, Secale cornutum 15x, Sepia 15x, Stramonium 15x, Tabacum 15x, Triticum repens 15x, Ustilago maidis 15x, Verbascum thapsus 15x, Lycopersicum esculentum 16x, Solanum nigrum 16x, Solanum tuberosum 16x, Stigmata maidis 16x, Torula cerevisiae 16x.

OTC - PURPOSE SECTION

Formulated for symptoms associated with sensitivity and intolerance to dairy, grain and nightshade foods such as bloating, headache, indigestion, itching and eruptions.

INACTIVE INGREDIENT SECTION

Inactive Ingredients: USP Purified Water; USP Gluten-free, non-GMO, organic cane alcohol 20%.

QUESTIONS SECTION

newtonlabs.net - Questions? 800.448.7256

Newton Laboratories, Inc. FDA Est # 1051203 Conyers, GA 30013

WARNINGS SECTION

WARNINGS: Keep out of reach of children. Do not use if tamper-evident seal is broken or missing. If symptoms worsen or persist for more than a few days, consult a doctor. If pregnant or breast-feeding, ask a doctor before use.

OTC - PREGNANCY OR BREAST FEEDING SECTION

If pregnant or breast-feeding, ask a doctor before use.

OTC - KEEP OUT OF REACH OF CHILDREN SECTION

Keep out of reach of children.